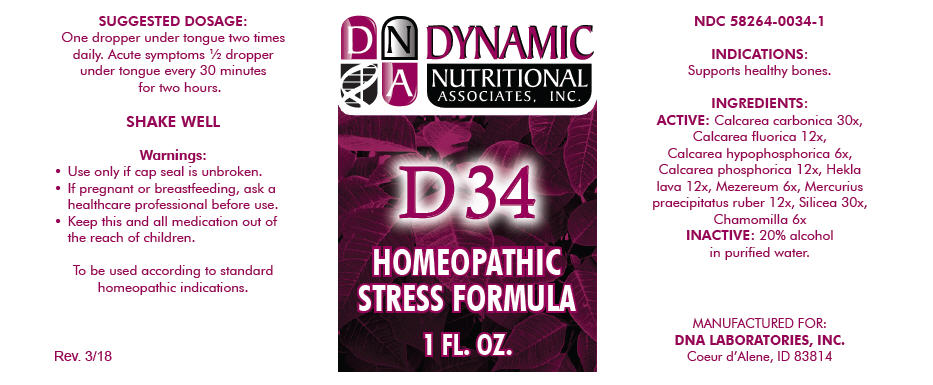 DRUG LABEL: D-34
NDC: 58264-0034 | Form: SOLUTION
Manufacturer: DNA Labs, Inc.
Category: homeopathic | Type: HUMAN OTC DRUG LABEL
Date: 20250113

ACTIVE INGREDIENTS: OYSTER SHELL CALCIUM CARBONATE, CRUDE 30 [hp_X]/1 mL; CALCIUM FLUORIDE 12 [hp_X]/1 mL; CALCIUM HYPOPHOSPHITE 6 [hp_X]/1 mL; TRIBASIC CALCIUM PHOSPHATE 12 [hp_X]/1 mL; HEKLA LAVA 12 [hp_X]/1 mL; DAPHNE MEZEREUM BARK 6 [hp_X]/1 mL; MERCURIC OXIDE 12 [hp_X]/1 mL; SILICON DIOXIDE 30 [hp_X]/1 mL; MATRICARIA CHAMOMILLA 6 [hp_X]/1 mL
INACTIVE INGREDIENTS: ALCOHOL; WATER

D-34

NDC 58264-0034-1

INDICATIONS

PURPOSE

Supports healthy bones.

INGREDIENTS

ACTIVE

Calcarea carbonica 30x, Calcarea fluorica 12x, Calcarea hypophosphorica 6x, Calcarea phosphorica 12x, Hekla lava 12x, Mezereum 6x, Mercurius praecipitatus ruber 12x, Silicea 30x, Chamomilla 6x

INACTIVE

20% alcohol in purified water.

SUGGESTED DOSAGE

One dropper under tongue two times daily. Acute symptoms ½ dropper under tongue every 30 minutes for two hours.

STORAGE AND HANDLING

SHAKE WELL

Warnings

- Use only if cap seal is unbroken.

PREGNANCY OR BREAST FEEDING

- If pregnant or breastfeeding, ask a healthcare professional before use.

KEEP OUT OF REACH OF CHILDREN

- Keep this and all medication out of the reach of children.

To be used according to standard homeopathic indications.

PRINCIPAL DISPLAY PANEL - 1 FL. OZ. Bottle Label

DYNAMIC
NUTRITIONAL
ASSOCIATES, INC.

D 34

HOMEOPATHIC
STRESS FORMULA

1 FL. OZ.